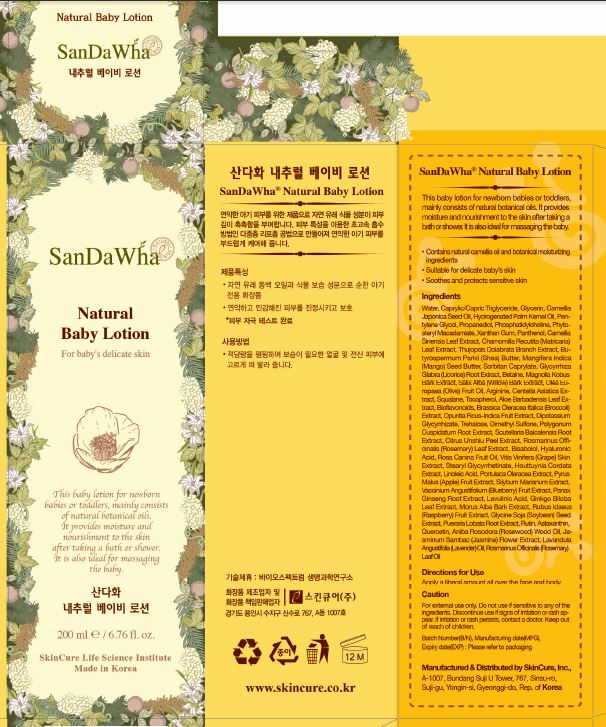 DRUG LABEL: SanDaWha Moisturizing Baby
NDC: 72289-0005 | Form: LOTION
Manufacturer: SKINCURE INC
Category: otc | Type: HUMAN OTC DRUG LABEL
Date: 20190224

ACTIVE INGREDIENTS: GLYCERIN 4.305 g/100 mL
INACTIVE INGREDIENTS: PANTHENOL; SQUALENE; WATER

Drug Facts

ACTIVE INGREDIENT

glycerin

INACTIVE INGREDIENT

Water(Aqua)
Caprylic/Capric Triglyceride
Glycerin
Camellia Japonica Seed Oil
Hydrogenated Palm Kernel Oil
Pentylene Glycol
Propanediol
Phosphatidylcholine
Phytosteryl Macadamiate
Panthenol
Camellia Sinensis Leaf Extract
Chamomilla Recutita (Matricaria) Leaf Extract
Thujopsis Dolabrata Branch Extract
Butyrospermum Parkii (Shea) Butter
Mangifera Indica (Mango) Seed Butter
Xanthan Gum
Sorbitan Caprylate
Glycyrrhiza Glabra (Licorice) Root Extract
Arginine
Betaine
Magnolia Kobus Bark Extract
Salix Alba (Willow) Bark Extract
Olea Europaea (Olive) Fruit Oil
Centella Asiatica Extract
Squalane
Tocopherol
Opuntia Ficus-Indica Fruit Extract
Dipotassium Glycyrrhizate
Trehalose
Aloe Barbadensis Leaf Extract
Dimethyl Sulfone
Polygonum Cuspidatum Root Extract
Scutellaria Baicalensis Root Extract
Citrus Unshiu Peel Extract
Rosmarinus Officinalis (Rosemary) Leaf Extract
Bisabolol
Hyaluronic Acid
Rosa Canina Fruit Oil
Vitis Vinifera (Grape) Skin Extract
Stearyl Glycyrrhetinate
Bioflavonoids
Houttuynia Cordata Extract
Linoleic Acid
Portulaca Oleracea Extract
Pyrus Malus (Apple) Fruit Extract
Silybum Marianum Extract
Vaccinium Angustifolium (Blueberry) Fruit Extract
Panax Ginseng Root Extract
Levulinic Acid
Ginkgo Biloba Leaf Extract
Morus Alba Bark Extract
Rubus Idaeus (Raspberry) Fruit Extract
Brassica Oleracea Italica (Broccoli) Extract
Glycine Soja (Soybean) Seed Extract
Pueraria Lobata Root Extract
Rutin
Astaxanthin
Quercetin
Aniba Rosodora (Rosewood) Wood Oil
Jasminum Sambac (Jasmine) Flower Extract
Lavandula Angustifolia (Lavender) Oil
Rosmarinus Officinalis (Rosemary) Leaf Oil

PURPOSE

soothes and protects sensitive skin

keep out of reach of the children

INDICATIONS AND USAGE

Gently massage into skin as often as needed

WARNINGS

for external use only

do not use if sensitive to any of the ingredients

discontinue use if signs of irritation or rash appear

if irritation or rash persists, contact a doctor

DOSAGE AND ADMINISTRATION

for external use only